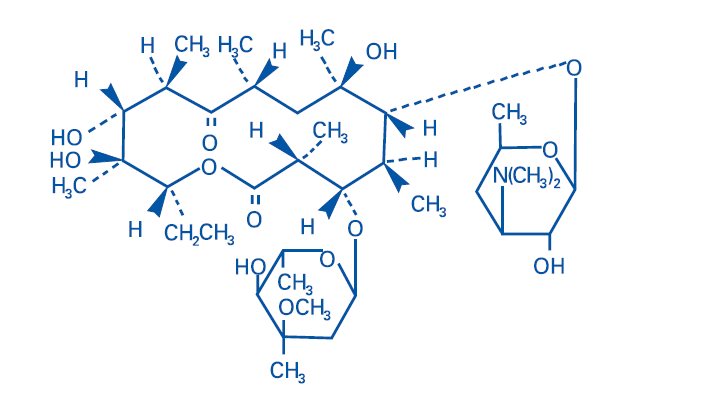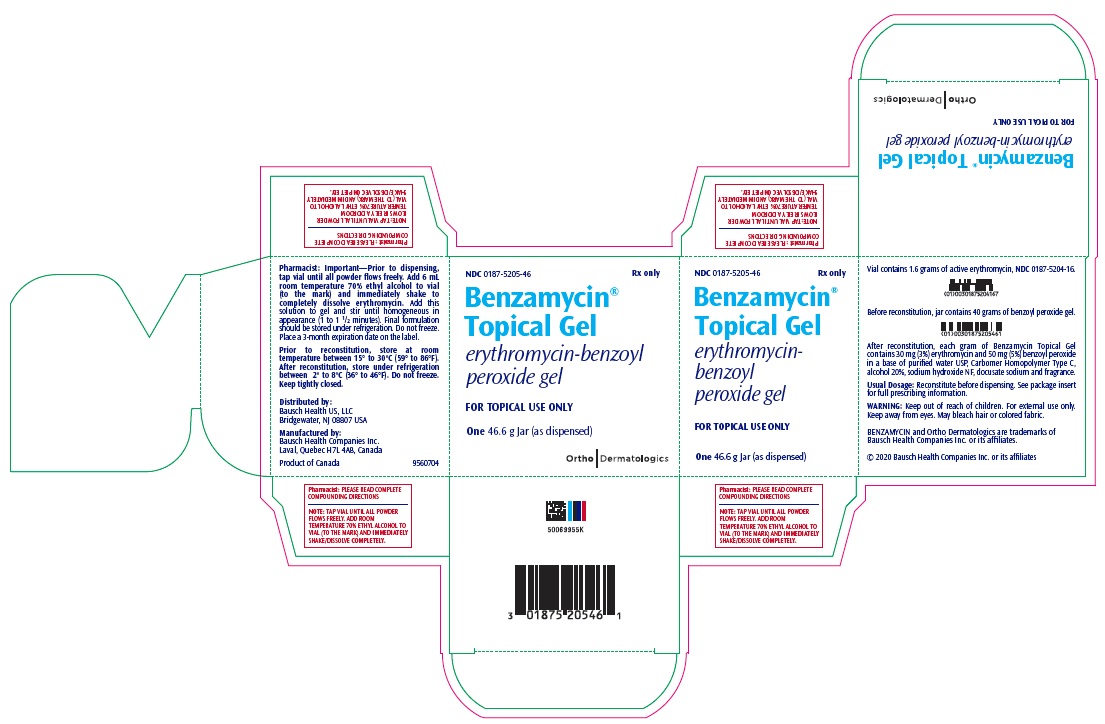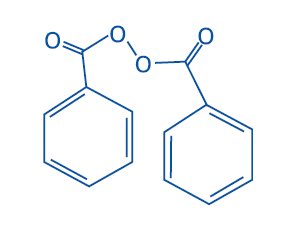 DRUG LABEL: Benzamycin
NDC: 0187-5205 | Form: KIT | Route: TOPICAL
Manufacturer: Bausch Health US, LLC
Category: prescription | Type: HUMAN PRESCRIPTION DRUG LABEL
Date: 20201130

ACTIVE INGREDIENTS: erythromycin 30 mg/1 g; benzoyl peroxide 50 mg/1 g
INACTIVE INGREDIENTS: water; CARBOMER HOMOPOLYMER TYPE C (ALLYL PENTAERYTHRITOL CROSSLINKED); alcohol; sodium hydroxide; docusate sodium

Benzamycin® Topical Gel
(erythromycin-benzoyl peroxide gel)

Topical Gel: erythromycin (3%), benzoyl peroxide (5%)
For Topical Use Only – Not for Ophthalmic Use
Reconstitute Before Dispensing

DESCRIPTION

Benzamycin® Topical Gel contains erythromycin [(3R*,4S*,5S*,6R*, 7R*, 9R*, 11R*, 12R*, 13S*, 14R*)-4-[(2,6-Dideoxy-3-C-methyl-3-O-methyl-α-L-ribo-hexopyranosyl)-oxy]-14-ethyl-7,12,13-trihydroxy-3,5,7,9,11,13-hexamethyl-6-[[3,4,6-trideoxy-3-(dimethylamino)-β-D-xylo-hexopyranosyl]oxy]oxacyclotetradecane-2,10-dione]. Erythromycin is a macrolide antibiotic produced from a strain of Saccharopolyspora erythraea (formerly Streptomyces erythreus). It is a base and readily forms salts with acids.

Chemically erythromycin is C37H67NO13. It has the following structural formula:

Erythromycin has the molecular weight of 733.94. It is a white crystalline powder and has a solubility of approximately 1 mg/mL in water and is soluble in alcohol at 25°C.

Benzamycin Topical Gel also contains benzoyl peroxide for topical use. Benzoyl peroxide is an antibacterial and keratolytic agent.

Chemically benzoyl peroxide is C14H10O4. It has the following structural formula:

Benzoyl peroxide has the molecular weight of 242.23. It is a white granular powder and is sparingly soluble in water and alcohol and soluble in acetone, chloroform and ether.

Each gram of Benzamycin Topical Gel contains, as dispensed, 30 mg (3%) of erythromycin and 50 mg (5%) of benzoyl peroxide in a base of purified water USP, Carbomer Homopolymer Type C, alcohol 20%, sodium hydroxide NF, docusate sodium and fragrance.

CLINICAL PHARMACOLOGY

The exact mechanism by which erythromycin reduces lesions of acne vulgaris is not fully known; however, the effect appears to be due in part to the antibacterial activity of the drug.

Benzoyl peroxide has a keratolytic and desquamative effect which may also contribute to its efficacy. Benzoyl peroxide has been shown to be absorbed by the skin where it is converted to benzoic acid.

MICROBIOLOGY

Erythromycin acts by inhibition of protein synthesis in susceptible organisms by reversibly binding to 50 S ribosomal subunits, thereby inhibiting translocation of aminoacyl transfer-RNA and inhibiting polypeptide synthesis. Antagonism has been demonstrated in vitro between erythromycin, lincomycin, chloramphenicol and clindamycin.

Benzoyl peroxide is an antibacterial agent which has been shown to be effective against Propionibacterium acnes, an anaerobe found in sebaceous follicles and comedones. The antibacterial action of benzoyl peroxide is believed to be due to the release of active oxygen.

INDICATIONS AND USAGE

Benzamycin Topical Gel is indicated for the topical treatment of acne vulgaris.

CONTRAINDICATIONS

Benzamycin Topical Gel is contraindicated in those individuals who have shown hypersensitivity to any of its components.

WARNINGS

Pseudomembranous colitis has been reported with nearly all antibacterial agents, including erythromycin, and may range in severity from mild to life-threatening. Therefore, it is important to consider this diagnosis in patients who present with diarrhea subsequent to the administration of antibacterial agents.

Treatment with antibacterial agents alters the normal flora of the colon and may permit overgrowth of clostridia. Studies indicate that a toxin produced by Clostridium difficile is one primary cause of “antibiotic-associated colitis”.

After the diagnosis of pseudomembranous colitis has been established, therapeutic measures should be initiated. Mild cases of pseudomembranous colitis usually respond to drug discontinuation alone. In moderate to severe cases, consideration should be given to management with fluids and electrolytes, protein supplementation and treatment with an antibacterial drug clinically effective against C. difficile colitis.

PRECAUTIONS

General:

For topical use only; not for ophthalmic use. Concomitant topical acne therapy should be used with caution because a possible cumulative irritancy effect may occur, especially with the use of peeling, desquamating or abrasive agents. If severe irritation develops, discontinue use and institute appropriate therapy.

The use of antibiotic agents may be associated with the overgrowth of nonsusceptible organisms including fungi. If this occurs, discontinue use and take appropriate measures.

Avoid contact with eyes and all mucous membranes.

Information for Patients:

Patients using Benzamycin Topical Gel should receive the following information and instructions:

1. This medication is to be used as directed by the physician. It is for external use only. Avoid contact with the eyes, nose, mouth, and all mucous membranes.
2. This medication should not be used for any disorder other than that for which it was prescribed.
3. Patients should not use any other topical acne preparation unless otherwise directed by their physician.
4. Patients should report to their physician any signs of local adverse reactions.
5. Benzamycin Topical Gel may bleach hair or colored fabric.
6. Keep product refrigerated and discard after 3 months.

CARCINOGENESIS, MUTAGENESIS, IMPAIRMENT OF FERTILITY

Data from a study using mice known to be highly susceptible to cancer suggests that benzoyl peroxide acts as a tumor promoter. The clinical significance of this is unknown.

No animal studies have been performed to evaluate the carcinogenic and mutagenic potential or effects on fertility of topical erythromycin. However, long-term (2-year) oral studies in rats with erythromycin ethylsuccinate and erythromycin base did not provide evidence of tumorigenicity. There was no apparent effect on male or female fertility in rats fed erythromycin (base) at levels up to 0.25% of diet.

Pregnancy:

Teratogenic Effects:

Animal reproduction studies have not been conducted with Benzamycin Topical Gel or benzoyl peroxide.

There was no evidence of teratogenicity or any other adverse effect on reproduction in female rats fed erythromycin base (up to 0.25% diet) prior to and during mating, during gestation and through weaning of two successive litters.

There are no well-controlled trials in pregnant women with Benzamycin Topical Gel. It also is not known whether Benzamycin Topical Gel can cause fetal harm when administered to a pregnant woman or can affect reproductive capacity. Benzamycin Topical Gel should be given to a pregnant woman only if clearly needed.

Nursing Women:

It is not known whether Benzamycin Topical Gel is excreted in human milk after topical application. However, erythromycin is excreted in human milk following oral and parenteral erythromycin administration. Therefore, caution should be exercised when erythromycin is administered to a nursing woman.

Pediatric Use:

Safety and effectiveness of this product in pediatric patients below the age of 12 have not been established.

ADVERSE REACTIONS

In controlled clinical trials, the incidence of adverse reactions associated with the use of Benzamycin Topical Gel was approximately 3%. These were dryness and urticarial reaction.

The following additional local adverse reactions have been reported occasionally: irritation of the skin including peeling, itching, burning sensation, erythema, inflammation of the face, eyes and nose, and irritation of the eyes. Skin discoloration, oiliness and tenderness of the skin have also been reported.

To report SUSPECTED ADVERSE REACTIONS, contact Bausch Health US, LLC at 1-800-321-4576 or FDA at 1-800-FDA-1088 or www.fda.gov/medwatch.

DOSAGE AND ADMINISTRATION

Benzamycin Topical Gel should be applied twice daily, morning and evening, or as directed by a physician, to affected areas after the skin is thoroughly washed, rinsed with warm water and gently patted dry.

How Supplied and Compounding Directions:

Size |  | Benzoyl; Peroxide Gel | Active Erythromycin; Powder; (In Plastic Vial) | 70% Ethyl Alcohol; To Be; Added
(Net Weight) | NDC | Benzoyl; Peroxide Gel | Active Erythromycin; Powder; (In Plastic Vial) | 70% Ethyl Alcohol; To Be; Added
46.6 grams | 0187-5205-46 | 40 grams | 1.6 grams | 6 mL
(as dispensed)

Prior to dispensing, tap vial until all powder flows freely. Add indicated amount of room temperature 70% ethyl alcohol to vial (to the mark) and immediately shake to completely dissolve erythromycin. Add this solution to gel and stir until homogeneous in appearance (1 to 1½ minutes). Benzamycin Topical Gel should then be stored under refrigeration. Do not freeze. Place a 3-month expiration date on the label.

NOTE: Prior to reconstitution, store at room temperature between 15° to 30°C (59° to 86°F).

After reconstitution, store under refrigeration between 2° to 8°C (36° to 46°F).

Do not freeze. Keep tightly closed. Keep out of reach of children.

Distributed by:
Bausch Health US, LLC
Bridgewater, NJ 08807 USA

Manufactured by:
Bausch Health Companies Inc.
Laval, Quebec H7L 4A8, Canada

BENZAMYCIN is a trademark of Bausch Health Companies Inc. or its affiliates.

© 2020 Bausch Health Companies Inc. or its affiliates

PLEASE READ COMPLETE COMPOUNDING DIRECTIONS

NOTE: TAP VIAL UNTIL ALL POWDER FLOWS FREELY. ADD ROOM TEMPERATURE 70% ETHYL ALCOHOL TO VIAL (TO THE MARK) AND IMMEDIATELY SHAKE/DISSOLVE COMPLETELY.

Rev. 11/2020
9560802

PRINCIPAL DISPLAY PANEL - 46.6 g Jar Carton

NDC 0187-5205-46

Rx only

Benzamycin®
Topical Gel

erythromycin-benzoyl
peroxide gel

FOR TOPICAL USE ONLY

One 46.6 g Jar (as dispensed)

Ortho Dermatologics